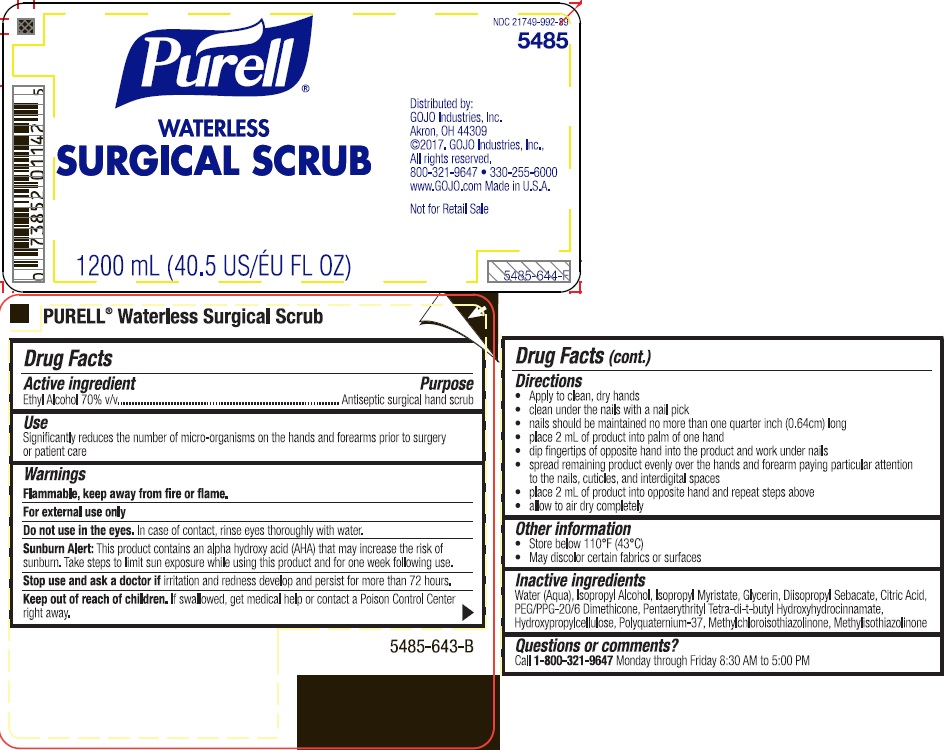 DRUG LABEL: PURELL Waterless Surgical Scrub
NDC: 21749-992 | Form: LIQUID
Manufacturer: GOJO Industries, Inc.
Category: otc | Type: HUMAN OTC DRUG LABEL
Date: 20241216

ACTIVE INGREDIENTS: ALCOHOL 0.7 mL/1 mL
INACTIVE INGREDIENTS: WATER; ISOPROPYL ALCOHOL; ISOPROPYL MYRISTATE; GLYCERIN; DIISOPROPYL SEBACATE; CITRIC ACID MONOHYDRATE; PENTAERYTHRITOL TETRAKIS(3-(3,5-DI-TERT-BUTYL-4-HYDROXYPHENYL)PROPIONATE); HYDROXYPROPYL CELLULOSE; METHYLCHLOROISOTHIAZOLINONE; METHYLISOTHIAZOLINONE

PURELL Waterless Surgical Scrub

Active ingredient

Ethyl alcohol 70% v/v

Purpose

Antiseptic surgical hand scrub

Uses

Significantly reduces the number of micro-organisms on the hands and forearms prior to surgery or patient care

Warnings

Flammable. Keep away from fire or flame.

For external use only

Sunburn Alert:This product contains an alpha hydroxy acid (AHA) that may increase the risk of sunburn. Take steps to limit sun exposure while using this product and for one week following use.

Do not use in the eyes.In case of contact, rinse eyes thoroughly with water.

Stop use and ask a doctor ifirritation and redness develop and persist for more than 72 hours.

Keep out of reach of children. If swallowed, get medical help or contact a Poison Control Center right away.

Directions

- clean under the nails with a nail pick
- mails should be maintained with a 1 millimeter free edge
- place 2 mL of product into palm of one hand
- dip fingers of opposite hand into the product and work under nails
- spread remaining product evenly over the hands and lower 2/3 of one forearm paying particular attention to the nails, cuticles, and interdigital spaces
- place 2 mL of product into opposite hand and repeat steps above
- allow to air dry completely

Inactive ingredients

Water (Aqua), Isopropyl Myristate, Glycerin, Diisopropyl Sebacate, Citric Acid, PEG/PPG-20/6 Dimethicone, Tetradibutyl Pentaerythrityl Hydroxyhydrocinnamate, Hydroxypropylcellulose, Polyquaternium-37, Methylchloroisothiazolinone, Methylisothiazolinone